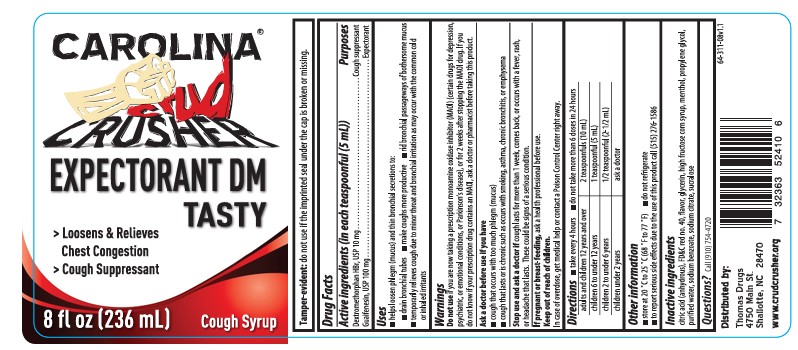 DRUG LABEL: Carolina Crud Crusher
NDC: 11383-311 | Form: SYRUP
Manufacturer: Weeks & Leo Co., Inc.
Category: otc | Type: HUMAN OTC DRUG LABEL
Date: 20251203

ACTIVE INGREDIENTS: GUAIFENESIN 200 mg/10 mL; DEXTROMETHORPHAN HYDROBROMIDE 20 mg/10 mL
INACTIVE INGREDIENTS: HIGH FRUCTOSE CORN SYRUP; GLYCERIN; MENTHOL; FD&C RED NO. 40; WATER; ANHYDROUS CITRIC ACID; PROPYLENE GLYCOL; SUCRALOSE; SODIUM CITRATE, UNSPECIFIED FORM; SODIUM BENZOATE

Expectorant DM Tasty Cough Syrup

ACTIVE INGREDIENT

Dextromethorphan HBr, USP 10 mg

Guaifenesin, USP 100 mg

in each teaspoonful (5 mL)

PURPOSE

Cough suppressant

Expectorant

Uses

- helps loosen phlegm (mucus) and thin bronchial secretions to:
- drain bronchial tubes
- make coughs more productive
- rid bronchial passageways of bothersome mucus
- temporarily relieve cough due to minor throat and bronchial irritation as may occur with the common cold or inhaled irritants

Do not use if you are now taking a prescription monoamine oxidase inhibitor (MAOI) (certain drugs for depression, psychiatric, or emotional conditions, or Parkinson's disease), or for 2 weeks after stopping the MAOI drug. If you do not know if your prescription drug contains an MAOI, ask a doctor or pharmacist before taking this product.

Ask a doctor before use if you have

- cough that occurs with too much phlegm (mucus)
- cough that lasts or is chronic such as occurs with smoking, asthma, chronic bronchitis, or emphysema

Stop use and ask a doctor if cough lasts for more than 1 week, comes back, or occurs with a fever, rash, or headache that lasts. These could be signs of a serious condition.

PREGNANCY OR BREAST FEEDING

If pregnant or breast-feeding, ask a health professional before use.

Keep out of reach of children.

In case of overdose, get medical help or contact a Poison Control Center right away.

Directions

- take every 4 hours
- do not take more than 6 doses in 24 hours

adults and children 12 years and over | 2 teaspoonfuls (10 mL)
children 6 to under 12 years | 1 teaspoonful (5 mL)
children 2 to under 6 years | 1/2 teaspoonful (2-1/2 mL)
children under 2 years | ask a doctor

Other information

- store at 20º C to 25º C (68º F 77º F)
- do not refrigerate
- to report serious side effects due to the use of this product call (515) 276-1586

INACTIVE INGREDIENT

citric acid (anhydrous), FD&C red no. 40, flavor, glycerin, high fructose corn syrup, menthol, propylene glycol, purified water, sodium benzoate, sodium citrate, sucralose

PACKAGE LABEL

Carolina Crud Crusher

Expectorant DM Tasty Cough Syrup

- Loosens & Relieves Chest Congestion
- Cough Suppressant